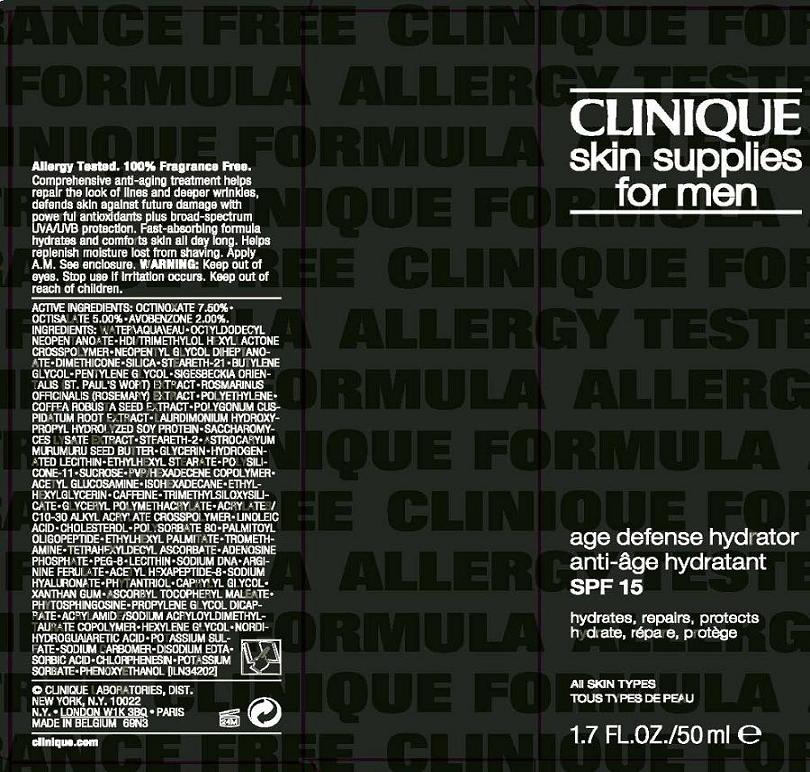 DRUG LABEL: CLINIQUE SKIN SUPPLIES FOR MEN AGE DEFENSE HYDRATOR
NDC: 49527-003 | Form: LOTION
Manufacturer: CLINIQUE LABORATORIES INC
Category: otc | Type: HUMAN OTC DRUG LABEL
Date: 20100730

ACTIVE INGREDIENTS: OCTINOXATE  7.5 mL/100 mL; OCTISALATE 5.0 mL/100 mL; AVOBENZONE 2.0 mL/100 mL

ACTIVE INGREDIENT

ACTIVE INGREDIENTS: octinoxate 7.50% [] octisalate 5.00% [] avobenzone 2.00%

WHEN USING

DIRECTIONS: APPLY AM

WARNINGS

WARNING: KEEP OUT OF EYES. STOP USE IF IRRITATION OCCURS. KEEP OUT OF REACH OF CHILDREN.

PACKAGE LABEL

PRINCIPAL DISPLAY PANEL

CLINIQUE
SKIN SUPPLIES FOR MEN
AGE DEFENSE HYDRATOR
SPF 15
ALL SKIN TYPES
1.7 FL OZ/ 50 ML
CLINIQUE LABORATORIES INC
NEW YORK, NY 10022